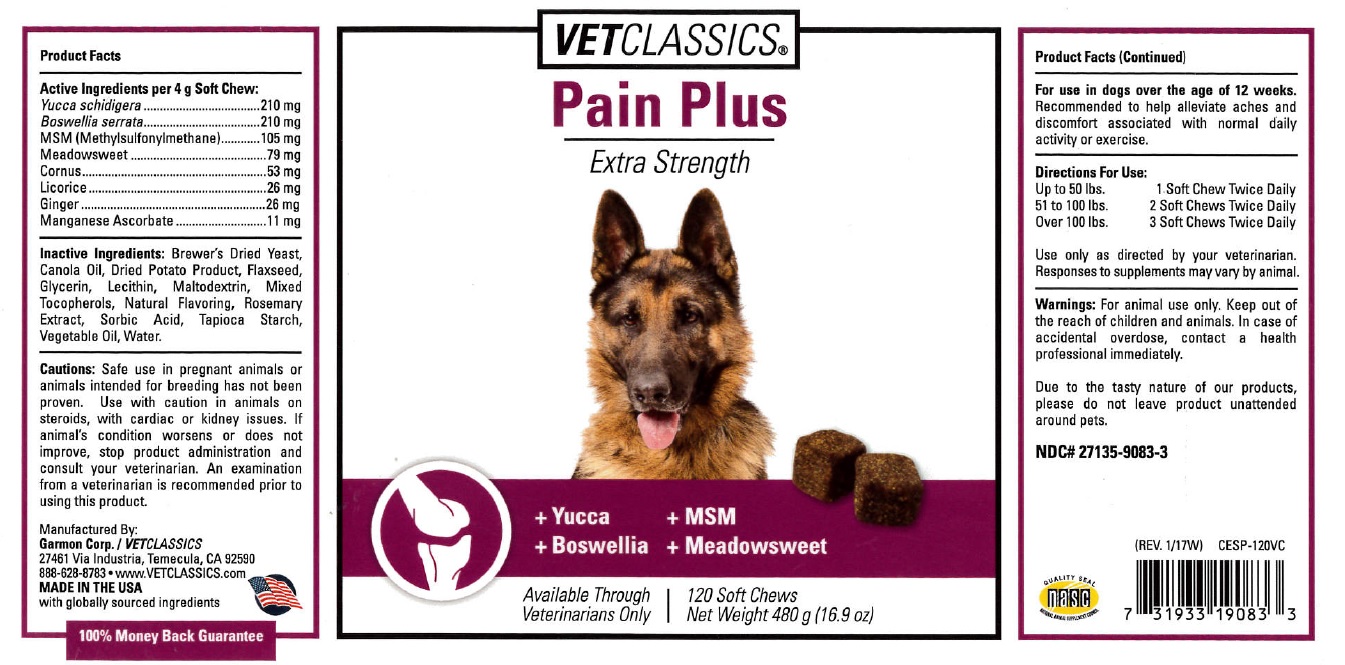 DRUG LABEL: CESP - Pain Plus Soft Chew
NDC: 27135-9083 | Form: PELLET
Manufacturer: Garmon Corp
Category: animal | Type: OTC ANIMAL DRUG LABEL
Date: 20170508

ACTIVE INGREDIENTS: YUCCA SCHIDIGERA 210 mg/4 g; BOSWELLIA SERRATA WHOLE 210 mg/4 g; DIMETHYL SULFONE 105 mg/4 g; FILIPENDULA ULMARIA WHOLE 79 mg/4 g; CORNUS ALBA WHOLE 53 mg/4 g; LICORICE 26 mg/4 g; GINGER 26 mg/4 g; MANGANESE ASCORBATE 11 mg/4 g
INACTIVE INGREDIENTS: YEAST, UNSPECIFIED; CANOLA OIL; POTATO; FLAX SEED; GLYCERIN; LECITHIN, SOYBEAN; MALTODEXTRIN; TOCOPHEROL; CHICKEN; ROSEMARY; SORBIC ACID; STARCH, TAPIOCA; CORN OIL; WATER

Vet Classics Pain Plus Soft Chews

Product Facts

Active Ingredients per 4 g Soft Chew:

Yucca Schindigera 210 mg

Boswellia serrata 210 mg

MSM (Methylsulfonylmethane) 105 mg

Meadowsweet 79 mg

Cornus 53 mg

Licorice 26 mg

Ginger 26 mg

Manganese Ascorbate 11 mg

INACTIVE INGREDIENT

Inactive Ingredients: Brewer's Dried Yeast, Canola Oil, Dried Potato Product, Flaxseed, Glycerin, Lecithin, Maltodextrin, Mixed Tocopherols, Natural Flavoring, Rosemary Extract, Sorbic Acid, Tapioca Starch, Vegetable Oil, Water.

WARNINGS AND PRECAUTIONS

Cautions: Safe use in pregnant animals or animals intended for breeding has not been proven. Use with caution in animals on steriods, with cardiac or kidney issues. If animal's condition worsens or does not improve, stop product administration and consult your veterinarian. An examination from a veterinarian is recommended prior to using this product.

Product Facts (Continued)

For use in dogs over the age of 12 weeks. Recommended to help alleviate aches and discomfort assiciated with normal daily activity or excercise.

DOSAGE AND ADMINISTRATION

Directions For Use:

Up to 50 lbs. 1 Soft Chew Twice Daily

51 to 100 lbs. 2 Soft Chews Twice Daily

Over 100 lbs. 3 Soft Chews Twice Daily

Use only as directed by your veterinarian. Responses to supplements may very by animal.

WARNINGS AND PRECAUTIONS

Warnings: For animal use only. Keep out of the reach of children and animals. Incase of accidental overdose, contact a health professional immediately.

Due to the tasty nature of our products, please do not leave product unattended around pets.